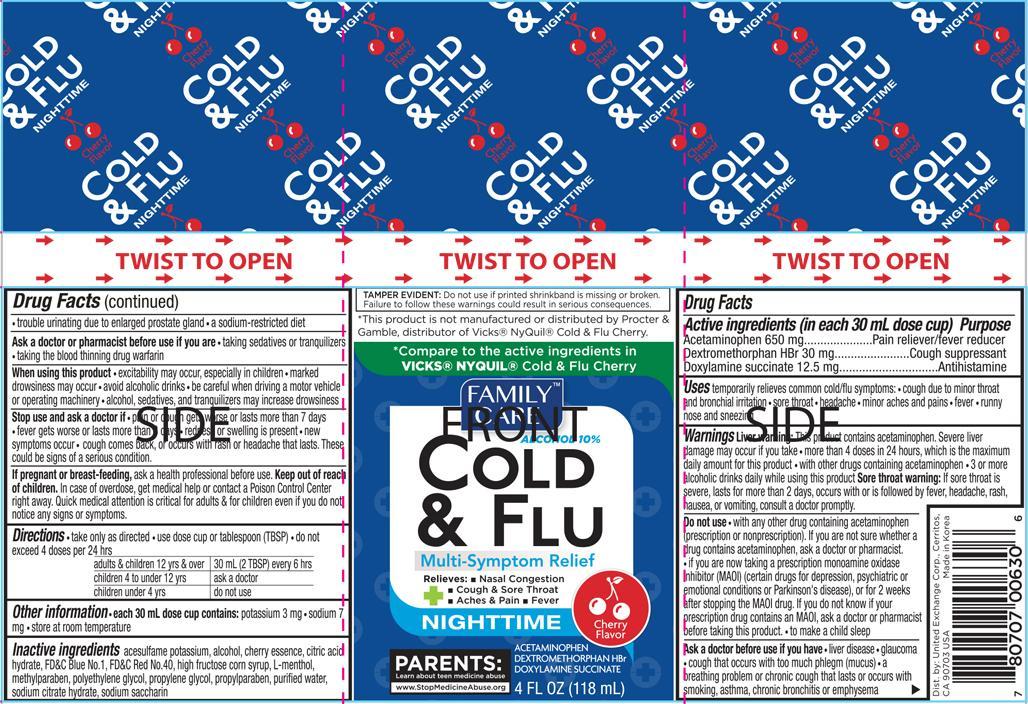 DRUG LABEL: Family Care Cold and Flu Multi Symptom
NDC: 65923-630 | Form: LIQUID
Manufacturer: United Exchange Corp.
Category: otc | Type: HUMAN OTC DRUG LABEL
Date: 20150730

ACTIVE INGREDIENTS: ACETAMINOPHEN 650 mg/30 mL; DEXTROMETHORPHAN HYDROBROMIDE 30 mg/30 mL; DOXYLAMINE SUCCINATE 12.5 mg/30 mL
INACTIVE INGREDIENTS: ACESULFAME POTASSIUM; ALCOHOL; CITRIC ACID MONOHYDRATE; FD&C BLUE NO. 1; FD&C RED NO. 40; HIGH FRUCTOSE CORN SYRUP; MENTHOL; METHYLPARABEN; POLYETHYLENE GLYCOLS; PROPYLENE GLYCOL; PROPYLPARABEN; WATER

ACTIVE INGREDIENT

Active ingredients (in each 30 mL dose cup) Purpose

Acetaminophen 650 mg...............................................Pain reliever/fever reducer

Dextromethorphan HBr 30 mg................................................Cough suppressant

Doxylamine succinate 12.5 mg.......................................................Antihistamine

Uses

temporarily relieves common cold/flu symptoms:

- cough due to minor throat and bronchial irritation
- sore throat
- headache
- minor aches and pains
- fever
- running nose and sneezing

Warnings

Liver warning: This product contains acetaminophen. Severe liver damage may occur if you take

- more than 4 doses in 24 hours, which is the maximum daily amount for this product
- with other drugs containing acetaminophen
- 3 or more alcoholic drinks daily while using this product

Sore throat warning: if sore throat is severe, lasts for more than 2 days, occurs with or is followed by fever, headache, rash, nausea, or vomiting, consult a doctor promptly.

Do not use

- with any other drug containing acetaminophen (prescription or nonprescription).
- If you are not sure whether a drug contains acetaminophen, ask a doctor or pharmacist.
- if you are now taking a presction monoamine oxidase inhibitor (MAOI) (certain drugs for depression, psychiatric or emotional conditions or Parkinson's disease), or for 2 weeks after stopping the MAOI drug. If you do not know if your prescription drug contains an MAOI, ask a doctor or pharmacist before taking this product.
- to make a child sleep

Ask a doctor before use if you have

- liver disease
- glaucoma
- cough that occurs with too much phlegm (mucus)
- a breathing problem or chronic cough that lasts or occurs with smoking, asthma, chronic bronchitis or emphysema
- trouble urinating due to enlarged prostate gland
- a sodium-restricted diet

Ask a doctor or pharmacist before use if you are

- taking sedatives or tranquilizers
- taking the blood thining drug warfarin

When using this product

- excitability may occur, especially in chldren
- marked drowsiness may occur
- avoid alcoholic drinks
- be careful when driving a motor vehicle or operating machinery
- alcohol, sedatives, and tranquilizers may increase drowsiness

Stop use and ask a doctor if

- pain or cough gets worse or lasts more than 7 days
- fever gets worse or lasts more than days
- redness or swelling is present
- new symptoms occur
- cough comes back, or occurs with rash or headache that lasts. These could be signs of a serious condition.

PREGNANCY OR BREAST FEEDING

If pregnant or breast-feeding, ask a health professional before use.

Keep out of reach of children. In case of overdose, get medical help or contact a Poison Control Center right away. Quick medical attention is critical for adults & for children even if you do not notice any signs or symptoms.

Directions

- take only as directed
- use dose cup or tablespoon (TBSP)
- do not exceed 4 doses per 24 hrs

adults & children 12 yrs & over | 30 mL (2 TBSP) every 6 hrs
children 4 to under 12 yrs | ask a doctor
children under 4 yrs | do not use

Other information

- each 30 mL dose cup contains:
- potassium 3 mg
- sodium 7 mg
- store at room temperature

Inactive ingredients

acesulfame potassium, alcohol, cherry essence, citric acid hydrate, FD&C Blue No. 1, FD&C Red No. 40, high fructose corn syrup, L-menthol, methylparaben, polyethylene glycol, propylene glycol, propylparaben, purified water, sodium citrate hydrate, sodium saccharin

DOSAGE AND ADMINISTRATION

Distributed by:

United Exchange Corp.

Cerritos, CA 90703 U.S.A.

Made in Korea